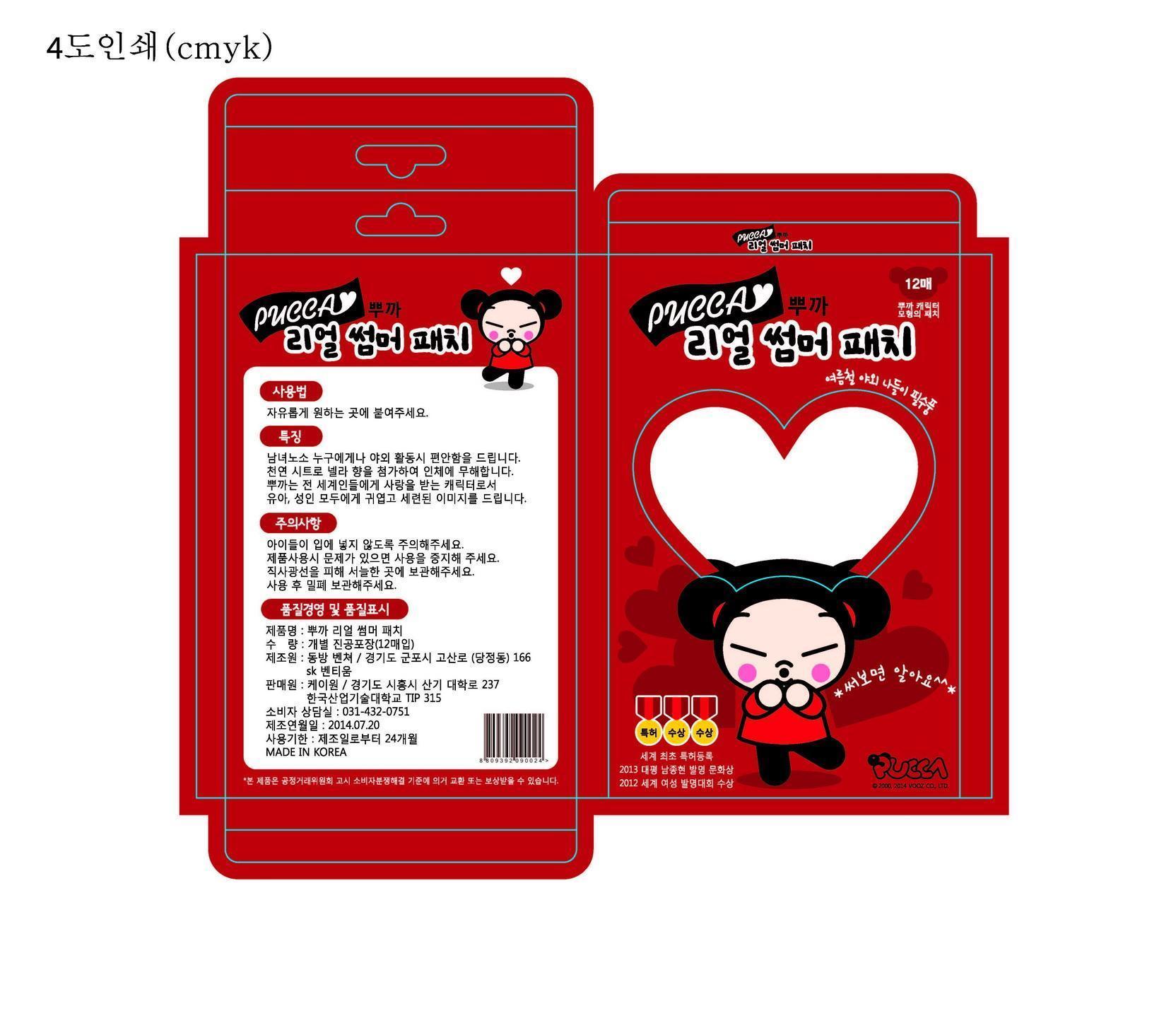 DRUG LABEL: REAL SUMMER 
NDC: 69449-1001 | Form: PATCH
Manufacturer: Kayone 
Category: otc | Type: HUMAN OTC DRUG LABEL
Date: 20141208

ACTIVE INGREDIENTS: SODIUM CHLORIDE 0.03 g/1 g
INACTIVE INGREDIENTS: WATER; IRON; CARBON DIOXIDE

Drug Facts

ACTIVE INGREDIENT

sodium chloride

INACTIVE INGREDIENT

iron powder, active carbon, resin vermiculite, salty water

PURPOSE

insect bite

keep out of reach of the children

INDICATIONS AND USAGE

When pasting on the mosquito, red ant or other inset bite area, pure mild fever soothes itching, and furthermore soothes festered skin.It can be used for men and women of all ages without adverse effects.Pucca is a character loved by people all around the world, which gives cute and refined image to both infants and adults.

WARNINGS

Be careful for children not to put it to the mouse. Stop using if there is any problem in the use of the product.Keep it in a cool area without direct light.Store it with sealing after the use. Be careful that if attachment and detachment are repeated, its adhesiveness may decrease.

DOSAGE AND ADMINISTRATION

for external use only